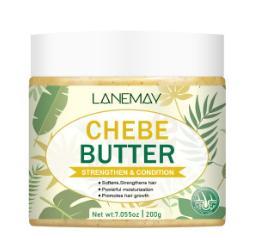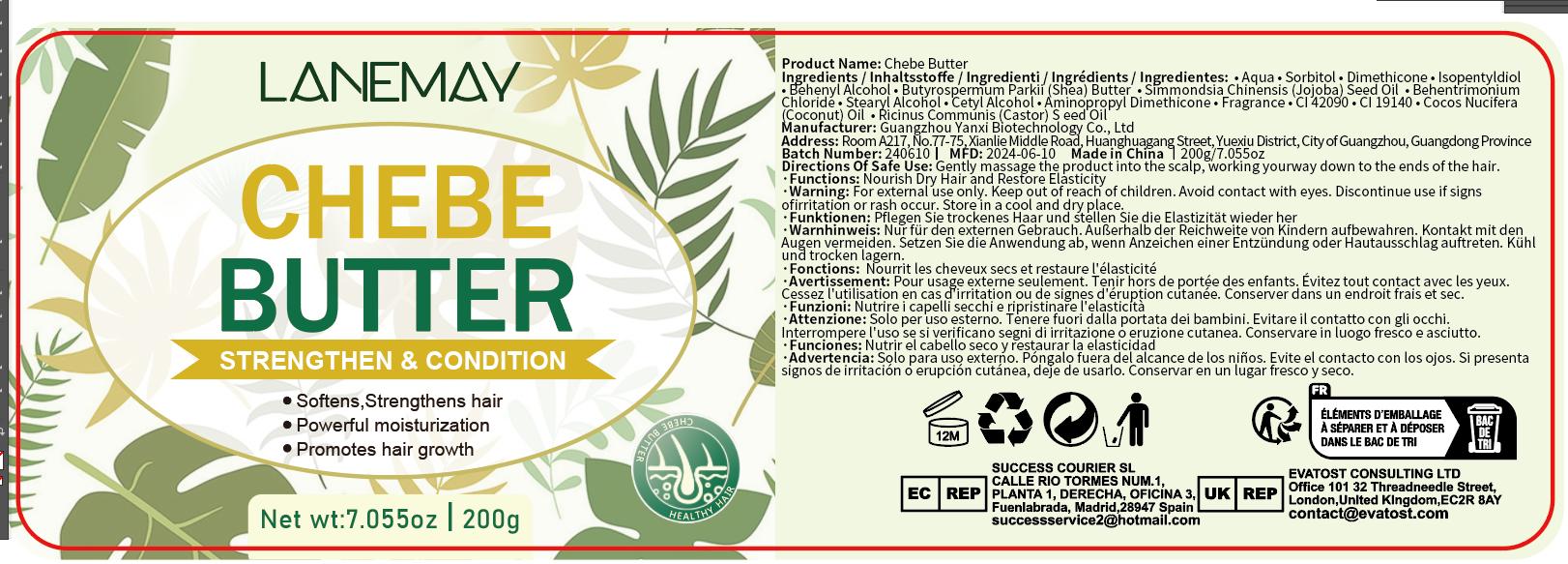 DRUG LABEL: Chebe Butter
NDC: 84025-056 | Form: CREAM
Manufacturer: Guangzhou Yanxi Biotechnology Co., Ltd
Category: otc | Type: HUMAN OTC DRUG LABEL
Date: 20240710

ACTIVE INGREDIENTS: SORBITOL 3 mg/200 g; DIMETHICONE 2 mg/200 g
INACTIVE INGREDIENTS: WATER

DOSAGE AND ADMINISTRATION

use as a normal hair cream

WARNINGS

keep out of children

INACTIVE INGREDIENT

aqua

INDICATIONS AND USAGE

for daily hair care

keep out of children

PURPOSE

strong and nourishing hair